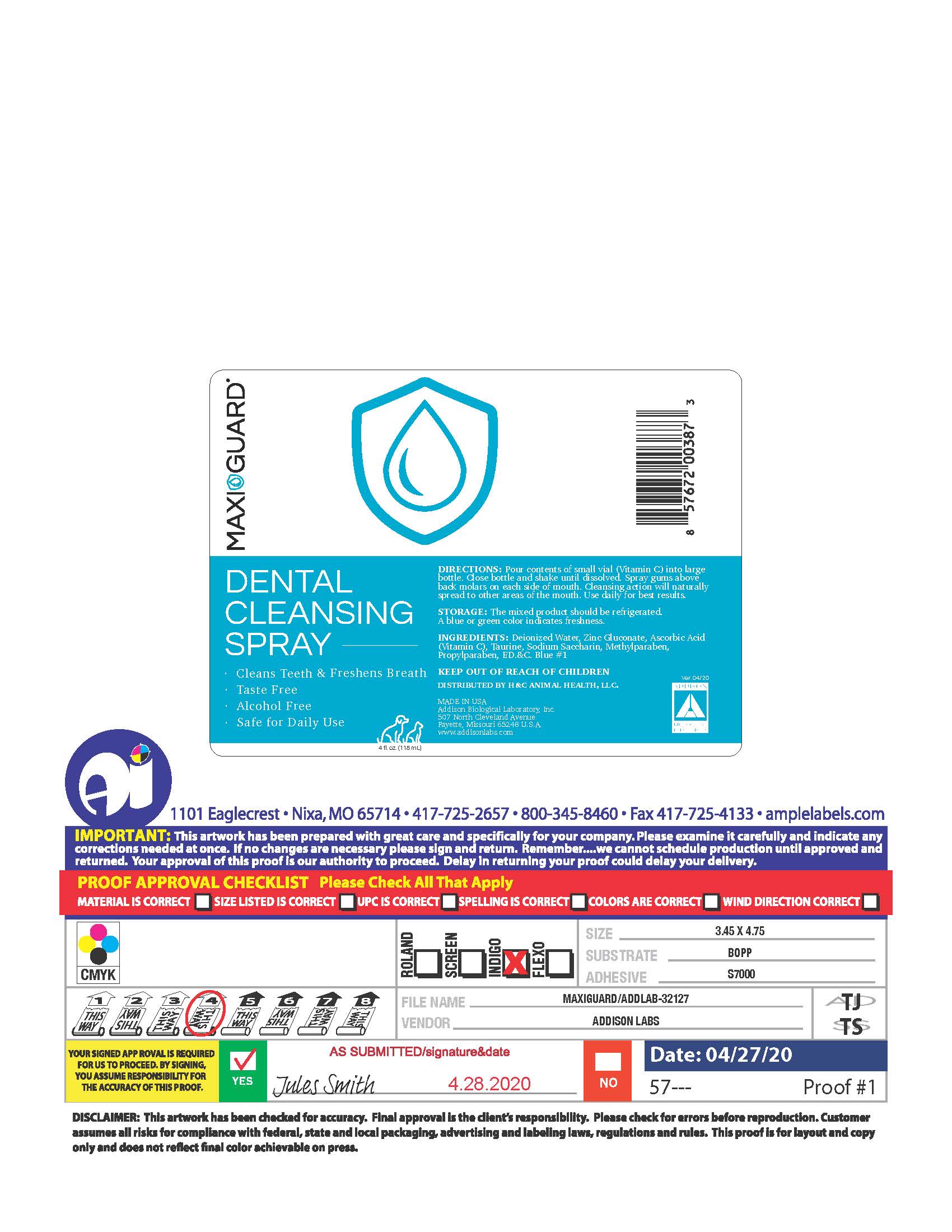 DRUG LABEL: MaxiGuard
NDC: 86137-4059 | Form: LIQUID
Manufacturer: H&C Animal Health, LLC.
Category: animal | Type: OTC ANIMAL DRUG LABEL
Date: 20251201

ACTIVE INGREDIENTS: ZINC GLUCONATE 0.022 g/1 mL
INACTIVE INGREDIENTS: WATER; ASCORBIC ACID; TAURINE; SACCHARIN SODIUM; METHYLPARABEN; PROPYLPARABEN; FD&C BLUE NO. 1

MaxiGuard Dental Cleansing Spray

DIRECTIONS

Pour contents of small vial (Vitamin C) into large bottle. Close bottle and shake until dissolved. Spray gums above back molars on each side of the mouth. Cleansing action will naturally spread to other areas of the mouth. Use daily for best results.

STORAGE

The mixed product should be refrigerated. A Blue or Green color denotes freshness.

INACTIVE INGREDIENT

INGREDIENTS

Deionized Water, Zinc Gluconate, Ascorbic Acid (Vitamin C), Taurine, Sodium Saccharin, Methylparaben, Propylparaben, F.D.&C. Blue #1.

PACKAGE LABEL

MAXIGUARD®
DENTAL CLEANSING SPRAY
Cleans Teeth & Freshens Breath
Taste Free

Alchol Free

Safe for Daily Use

Canine / Feline

DIRECTIONS
Pour contents of small vial (Vitamin C) into large bottle. Close bottle and shake until dissolved. Spray gums above back molars on each side of the mouth. Cleansing action will naturally spread to other areas of the mouth. Use daily for best results.
STORAGE
The mixed product should be refrigerated. A Blue or Green color denotes freshness.
INGREDIENTS:
Deionized Water, Zinc Gluconate, Ascorbic Acid (Vitamin C), Taurine, Sodium Saccharin, Methylparaben, Propylparaben, F.D.&C. Blue #1.
KEEP OUT OF REACH OF CHILDREN
4 FL. OZ. (118 mL)
DISTRIBUTED BY H&C ANIMAL HEALTH , LLC.

Made in the U.S.A.

Addison Biological Laboratory, Inc.

507 North Cleveland Avenue
Fayette, Missouri 65248
www.addisonlabs.com
REV. 04/20